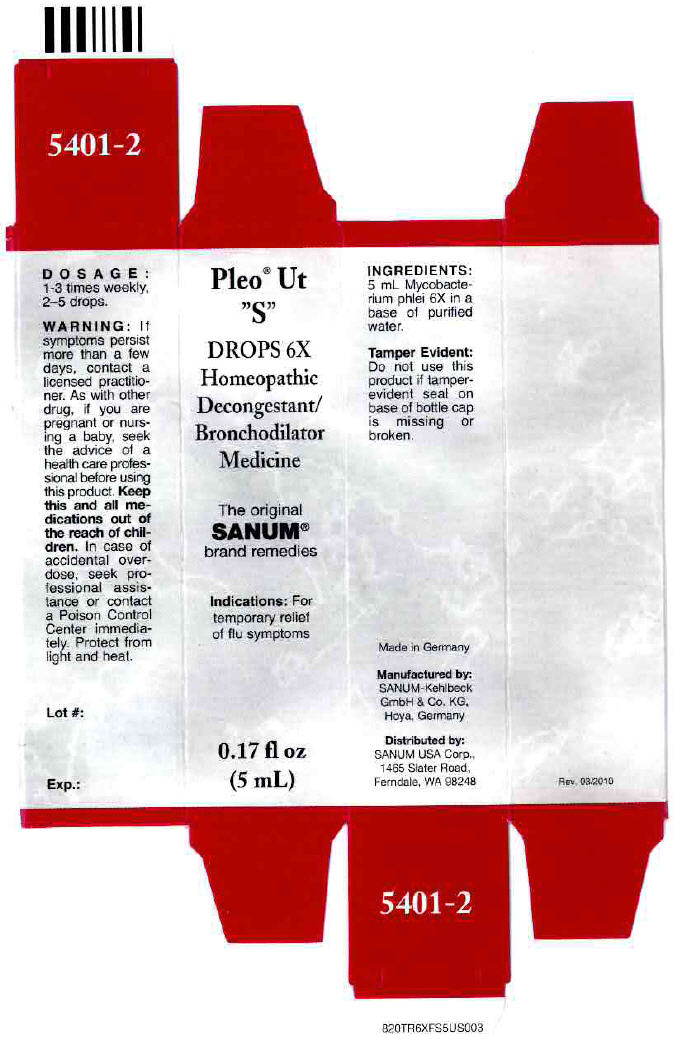 DRUG LABEL: Pleo Ut S
NDC: 60681-5401 | Form: SOLUTION/ DROPS
Manufacturer: Sanum Kehlbeck GmbH & Co. KG
Category: homeopathic | Type: HUMAN OTC DRUG LABEL
Date: 20120309

ACTIVE INGREDIENTS: mycobacterium phlei 6 [hp_X]/5 mL
INACTIVE INGREDIENTS: water

Pleo® Ut "S"
DROPS 6X

PURPOSE

Homeopathic Decongestant/Bronchodilator Medicine

0.17 fl oz
(5 mL)

Indications

For temporary relief of flu symptoms

ACTIVE INGREDIENT

INACTIVE INGREDIENT

INGREDIENTS

5 mL Mycobacterium phlei 6X in a base of purified water.

Tamper Evident

Do not use this product if tamper-evident seal on base of bottle cap is missing or broken.

DOSAGE

1-3 times weekly, 2–5 drops.

WARNING

If symptoms persist more than a few days, contact a licensed practitioner. As with other drug, if you are pregnant or nursing a baby, seek the advice of a health care professional before using this product.

KEEP OUT OF REACH OF CHILDREN

Keep this and all other medications out of the reach of children. In case of accidental overdose, seek professional assistance or contact a Poison Control Center immediately.

STORAGE AND HANDLING

Protect from light and heat.

Manufactured by:
SANUM-Kehlbeck
GmbH & Co. KG,
Hoya, Germany

Distributed by:
SANUM USA Corp.,
1465 Slater Road,
Ferndale, WA 98248

Rev. 03/2010

PRINCIPAL DISPLAY PANEL - 5 mL Carton

Pleo® Ut
"S"
DROPS 6X

Homeopathic
Decongestant/
Bronchodilator
Medicine

The original
SANUM®
brand remedies

Indications: For
temporary relief
of flu symptoms

0.17 fl oz
(5 mL)